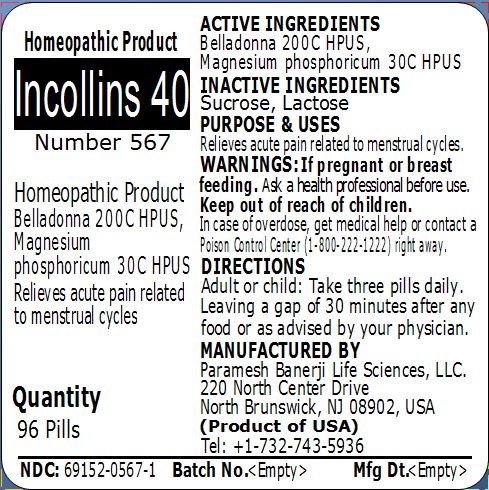 DRUG LABEL: Incollins 40 Number 567
NDC: 69152-0567 | Form: PELLET
Manufacturer: Paramesh Banerji Life Sciences LLC
Category: homeopathic | Type: HUMAN OTC DRUG LABEL
Date: 20150319

ACTIVE INGREDIENTS: ATROPA BELLADONNA 200 [hp_C]/1 1; MAGNESIUM PHOSPHATE, DIBASIC TRIHYDRATE 30 [hp_C]/1 1
INACTIVE INGREDIENTS: LACTOSE; SUCROSE

Active Ingredients

Belladonna 200C HPUS, Magnesium phosphoricum 30C HPUS

Inactive Ingredients

Sucrose, Lactose

Purpose

Relieves acute pain related to menstrual cycles

Uses

Relieves acute pain related to menstrual cycles

Warnings

If pregnant or breast feeding ask a health professional before use.

Keep out of reach of children. In case of overdose, get medical help or contact a Poison Control Center (1-800-222-1222) right away.

Direction

Adult or child: Take three pills daily. Leaving a gap of 30 minutes after any food or as advised by your physician.

Manufactured by

Paramesh Banerji Life Sciences, LLC

220 North Center Drive

North Brunswick, NJ 08902, USA

Product of USA

Tel: +1-732-743-5936

Principal Display Panel

Homeopathic Product

Incollins 40

Number 567

Homeopathic Product

Belladonna 200C HPUS, Magnesium phosphoricum 30C HPUS

Relieves acute pain related to menstrual cycles

Quantity

96 Pills